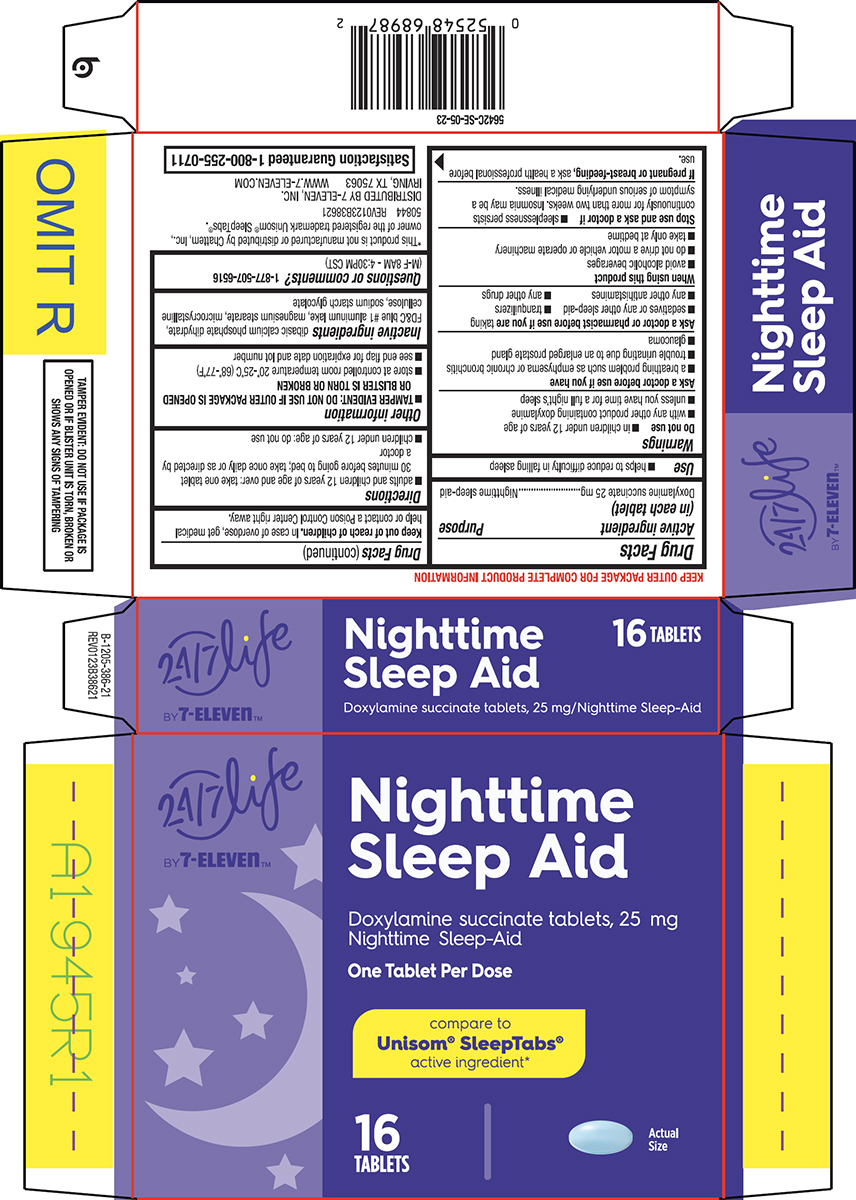 DRUG LABEL: Nighttime Sleep Aid
NDC: 50844-260 | Form: TABLET
Manufacturer: L.N.K. International, Inc.
Category: otc | Type: HUMAN OTC DRUG LABEL
Date: 20260106

ACTIVE INGREDIENTS: DOXYLAMINE SUCCINATE 25 mg/1 1
INACTIVE INGREDIENTS: DIBASIC CALCIUM PHOSPHATE DIHYDRATE; FD&C BLUE NO. 1 ALUMINUM LAKE; MAGNESIUM STEARATE; MICROCRYSTALLINE CELLULOSE; SODIUM STARCH GLYCOLATE TYPE A POTATO

Convenience Valet 44-386

Active ingredient (in each tablet)

Doxylamine succinate 25 mg

Purpose

Nighttime sleep-aid

Use

- helps to reduce difficulty in falling asleep

Warnings

Do not use

- in children under 12 years of age
- with any other product containing doxylamine
- unless you have time for a full night’s sleep

Ask a doctor before use if you have

- a breathing problem such as emphysema or chronic bronchitis
- trouble urinating due to an enlarged prostate gland
- glaucoma

Ask a doctor or pharmacist before use if you are

taking

- sedatives or any other sleep-aid
- tranquilizers
- any other antihistamines
- any other drugs

When using this product

- avoid alcoholic beverages
- do not drive a motor vehicle or operate machinery
- take only at bedtime

Stop use and ask a doctor if

- sleeplessness persists continuously for more than two weeks. Insomnia may be a symptom of serious underlying medical illness.

If pregnant or breast-feeding,

ask a health professional before use.

Keep out of reach of children.

In case of overdose, get medical help or contact a Poison Control Center right away.

Directions

- adults and children 12 years of age and over: take one tablet 30 minutes before going to bed; take once daily or as directed by a doctor
- children under 12 years of age: do not use

Other information

- TAMPER EVIDENT: DO NOT USE IF OUTER PACKAGE IS OPENED OR BLISTER IS TORN OR BROKEN
- store at controlled room temperature 20°-25°C (68°-77°F)
- see end flap for expiration date and lot number

Inactive ingredients

dibasic calcium phosphate dihydrate, FD&C blue #1 aluminum lake, magnesium stearate, microcrystalline cellulose, sodium starch glycolate

Questions or comments?

1-877-507-6516 (M-F 8AM - 4:30PM CST)

Principal display panel

24/7 Life

BY 7-Eleven™

Nighttime
Sleep Aid
Doxylamine succinate tablets, 25 mg
Nighttime Sleep-Aid

One Tablet Per Dose

compare to
Unisom® SleepTabs®
active ingredient*

16
TABLETS

Actual
Size

TAMPER EVIDENT: DO NOT USE IF PACKAGE IS
OPENED OR IF BLISTER UNIT IS TORN, BROKEN OR
SHOWS ANY SIGNS OF TAMPERING

*This product is not manufactured or distributed by Chattem, Inc.,
owner of the registered trademark Unisom® SleepTabs®.
50844 REV0123B38621

DISTRIBUTED BY 7-ELEVEN, INC.
IRVING, TX 75063 WWW.7-ELEVEN.COM

Satisfaction Guaranteed 1-800-255-0711

Convenience Valet 44-386